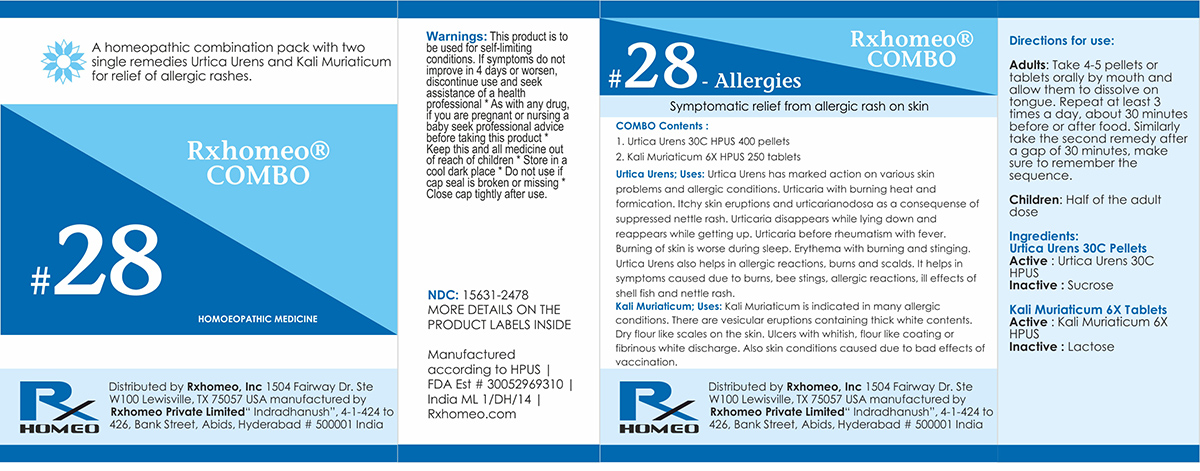 DRUG LABEL: Rxhomeo Homeopathic Combo
NDC: 15631-2478 | Form: KIT | Route: ORAL
Manufacturer: Rxhomeo Private Limited d.b.a.
Category: homeopathic | Type: HUMAN OTC DRUG LABEL
Date: 20161012

ACTIVE INGREDIENTS: URTICA URENS 1 [hp_X]/1 1; POTASSIUM CHLORIDE 1 [hp_X]/1 1
INACTIVE INGREDIENTS: SUCROSE; LACTOSE

ACTIVE INGREDIENT

URTICA URENS HPUS 1X and higher

KALI MURIATICUM HPUS 1X and Higher

USES

A homeopathic combination pack with two single remedies Urtica Urens and Kali Muriaticum for relief of allergic rashes.

Urtica Urens; Uses: Urtica Urens has marked action on various skin problems and allergic conditions. Urticaria with burning heat and formication. Itchy skin eruptions and urticaria nodosa as a consequense of suppressed nettle rash. Urticaria disappears while lying down and reappears while getting up. Urticaria before rheumatism with fever. Burning of skin is worse during sleep. Erythema with burning and stinging. Urtica Urens also helps in allergic reactions, burns and scalds. It helps in symptoms caused due to burns, bee stings, allergic reactions, ill effects of shell fish and nettle rash.

Kali Muriaticum; Uses: Kali Muriaticum is indicated in many allergic conditions. There are vesicular eruptions containing thick white contents. Dry flour like scales on the skin. Ulcers with whitish, flour like coating or fibrinous white discharge. Also skin conditions caused due to bad effects of vaccination.

INDICATIONS

Condition listed above or as directed by the physician

DOSAGE

PELLETS included in the Combo

Adults- Take 4 or 6 Pellets by mouth, three times daily or as suggested by physician. Children 2 years and older- take 1/2 the adult dose.

TABLETS included in the Combo

Adults- Take 4 or 6 Tablets by mouth, three times daily or as suggested by physician. Children 2 years and older- take 1/2 the adult dose.

WARNINGS

This product is to be used for self-limiting conditions

STOP USE

If symptoms do not improve in 4 days, or worsen, discontinue use and seek assistance of health professional

KEEP OUT OF REACH OF CHILDREN

Keep this and all medication out of reach of children

Do not use if capseal is broken or missing.

Close the cap tightly after use.

INACTIVE INGREDIENTS

Sucrose for Pellets.

Lactose for Tablets.

STORAGE

Store in a cool dark place

QUESTIONS OR COMMENTS

www.Rxhomeo.com | 1.888.2796642 | info@rxhomeo.com
Rxhomeo, Inc 1504 Fairway Dr. Ste W 100 Lewisville, TX 75057 USA